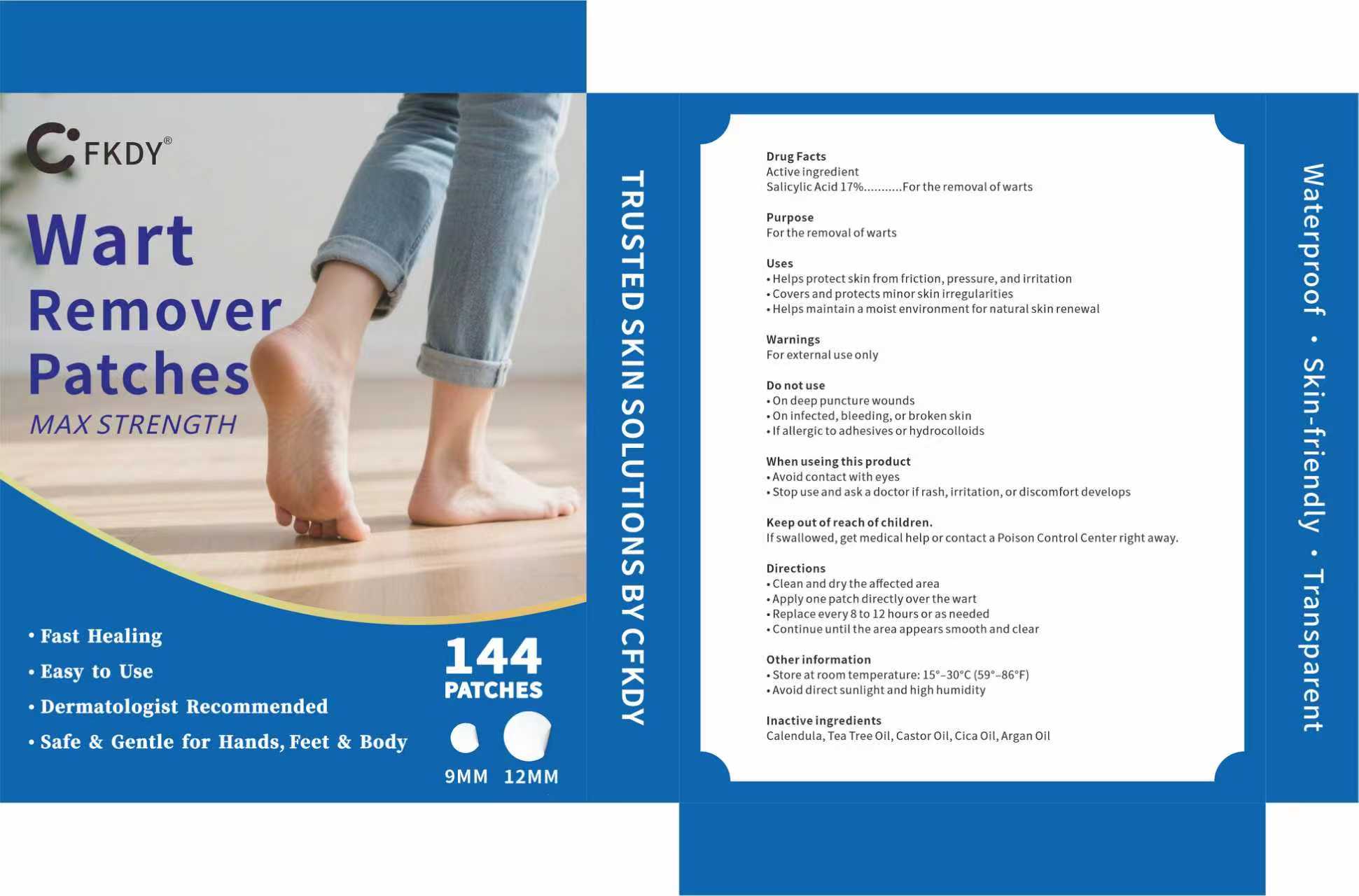 DRUG LABEL: Wart Remover Patches
NDC: 85593-011 | Form: PATCH
Manufacturer: Guangzhou ChuanMa International Trading Co.,Ltd.
Category: otc | Type: HUMAN OTC DRUG LABEL
Date: 20250902

ACTIVE INGREDIENTS: SALICYLIC ACID 17 g/100 g
INACTIVE INGREDIENTS: CENTELLA ASIATICA; CALENDULA OFFICINALIS FLOWERING TOP; TEA TREE OIL; CASTOR OIL; ARGAN OIL

ACTIVE INGREDIENT

Salicylic Acid 17%......For the removal ofwarts

PURPOSE

PurposeFor the removal ofwarts

Uses
.Helps protectskin from friction,pressure, and irritation.covers and protects minor skin irregularities.Helps maintain a moist environment for natural skin renewal

Warnings

For externaluse only

Do not use

On deep puncture wounds.

On infected,bleeding,

or broken skin.

lfallergic to adhesives or hydrocolloids

Keep out ofreach of children.
if swallowed, get medical help or contact a Poison Control Center right away.

Directions
.Clean and dry the affected area.Apply one patch directiy over the wartReplace every8 to 12 hours or as neededContinue until the area appears smooth and clear

Other information
.Store atroom temperature: 15-30°C(59°-86°F).Avoid direct sunlight and high humidity

INACTIVE INGREDIENT

Calendula,Tea Tree Oil, Castor Oil, Cica Oil, Argan Oil